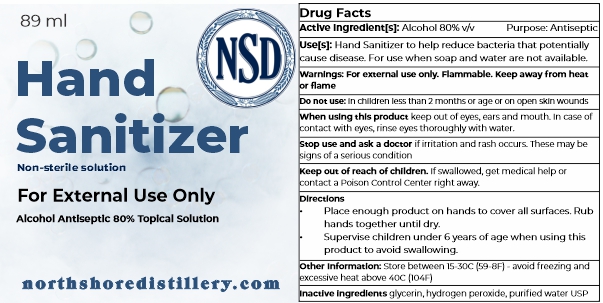 DRUG LABEL: NSD Hand Sanitizer
NDC: 73899-101 | Form: LIQUID
Manufacturer: North Shore Distillery, LLC
Category: otc | Type: HUMAN OTC DRUG LABEL
Date: 20200323

ACTIVE INGREDIENTS: ALCOHOL 80 mL/100 mL
INACTIVE INGREDIENTS: HYDROGEN PEROXIDE; GLYCERIN; WATER

Hand Sanitizer

Warnings:

For external use only. Flammable. Keep away from heat or flame

Active Ingredient(s)

Active Ingredients ………….……….….…………………..................... Purpose

Alcohol 80% v/v…….………….……….….………………….....................Antiseptic

Do not use

• in children less than 2 months of age

• on open skin wounds

When using this product keep out of eyes, ears, and mouth. In case of contact with eyes, rinse eyes thoroughly with water.

Stop use and ask a doctor if irritation or rash occurs. These may be signs of a serious condition.

Keep out of reach of children. If swallowed, get medical help or contact a Poison Control Center right away.

Inactive Ingredients

glycerin, hydrogen peroxide, purified water USP

Other Information

• Store between 15-30C (59-86F)

• Avoid freezing and excessive heat above 40C (104F)

Use(s)

Hand Sanitizer to help reduce bacteria that potentially can cause disease. For use when soap and water are not available.

Directions

• Place enough product on hands to cover all surfaces. Rub hands together until dry.

• Supervise children under 6 years of age when using this product to avoid swallowing.

Use(s)

Hand sanitizer to help reduce bacteria that potentially can cause disease. For use when soap and water are not available.